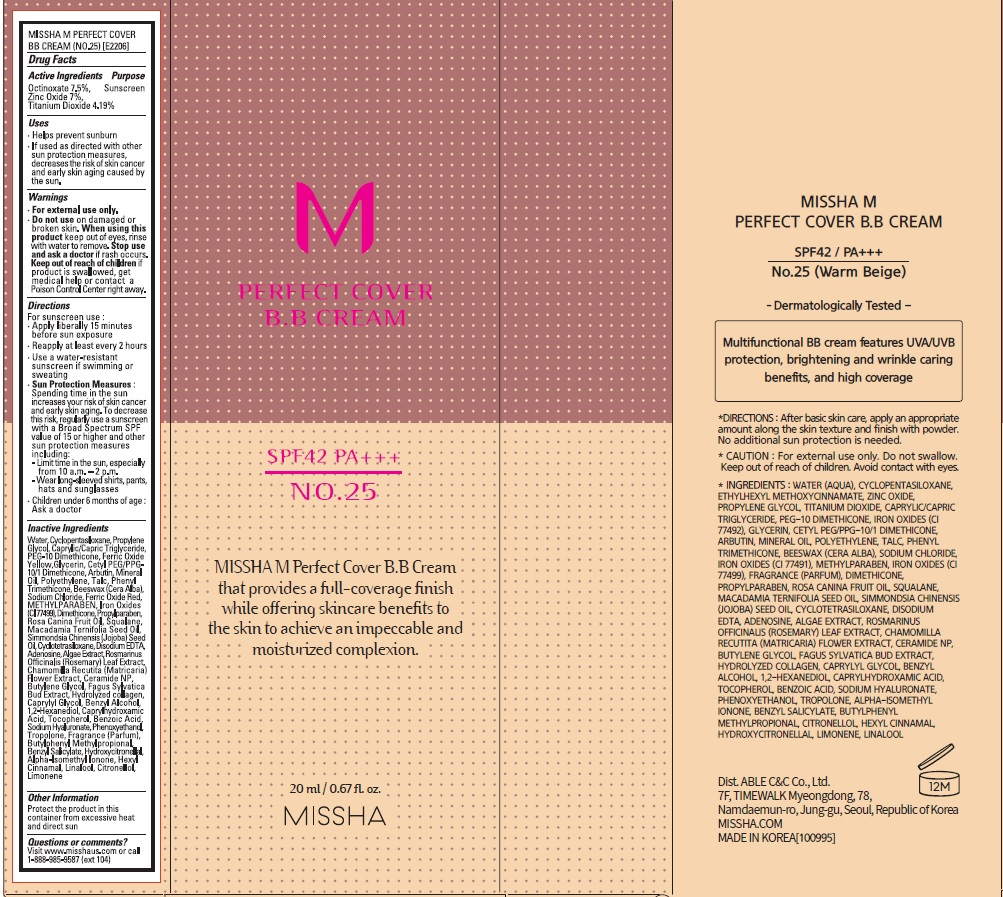 DRUG LABEL: MISSHA M Perfect Cover BB Cream SPF42 No. 25
NDC: 13733-246 | Form: CREAM
Manufacturer: Able C&C Co., Ltd.
Category: otc | Type: HUMAN OTC DRUG LABEL
Date: 20241205

ACTIVE INGREDIENTS: TITANIUM DIOXIDE 4.19 g/100 mL; ZINC OXIDE 7 g/100 mL; OCTINOXATE 7.5 g/100 mL
INACTIVE INGREDIENTS: PHENOXYETHANOL; TROPOLONE; SODIUM CHLORIDE; MACADAMIA OIL; HYALURONATE SODIUM; GLYCERIN; PROPYLENE GLYCOL; MEDIUM-CHAIN TRIGLYCERIDES; TALC; WATER; CYCLOMETHICONE; HIGH DENSITY POLYETHYLENE; FERRIC OXIDE YELLOW; CETYL PEG/PPG-10/1 DIMETHICONE (HLB 2); ARBUTIN; PEG-10 DIMETHICONE (600 CST); MINERAL OIL; TRIS(TRIMETHYLSILOXY)PHENYLSILANE; ABRONIA VILLOSA LEAF; PROPYLPARABEN; JOJOBA OIL; TOCOPHEROL; YELLOW WAX; CYCLOMETHICONE 4; LAMINARIA HYPERBOREA; CHAMOMILE FLOWER OIL; CERAMIDE AP; FERRIC OXIDE RED; METHYLPARABEN; FERROSOFERRIC OXIDE; DIMETHICONE; SQUALANE; EDETATE DISODIUM ANHYDROUS; ADENOSINE; ROSEMARY; BUTYLENE GLYCOL; FAGUS SYLVATICA FLOWER BUD; CAPRYLYL GLYCOL; BENZYL ALCOHOL; 1,2-HEXANEDIOL; CAPRYLHYDROXAMIC ACID; BENZOIC ACID

MISSHA M Perfect Cover BB Cream SPF42 (No. 25) 20mL

Active Ingredients

Octinoxate 7.5%, Active Ingredients: Zinc Oxide 7.0%, Titanium Dioxide 4.20%

Purpose

Sunscreen

Inactive Ingredients

Water (Aqua), Cyclomethicone, Propylene Glycol, Caprylic/Capric Triglyceride, PEG-10 Dimethicone, Iron Oxides (CI 77492), Cetyl PEG/PPG-10/1 Dimethicone, Arbutin, Mineral Oil, Glycerin, Polyethylene, Talc, Beeswax (Cera Alba), Phenyl Trimethicone, Sodium Chloride, Iron Oxides (CI 77491), Methylparaben, Iron Oxides (CI 77499), Dimethicone, Propylparaben, Rosa Canina Fruit Oil, Simmondsia Chinensis (Jojoba) Seed Oil, Squalane, Macadamia Ternifolia Seed Oil, Hydrolyzed Collagen, Disodium EDTA, Adenosine, Algae Extract, Rosmarinus Officinalis (Rosemary) Leaf Extract, Fagus Sylvatica Bud Extract, Sodium Hyaluronate, Ceramide 3, Chamomilla Recutita (Matricaria) Flower Extract, Fragrance (Parfum), Hydroxyisohexyl 3-Cyclohexene Carboxaldehyde, Butylphenyl Methylpropional, Benzyl Salicylate, Hydroxycitronellal, Alpha-Isomethyl Ionone, Hexyl Cinnamal, Linalool, Citronellol

Warnings

For external use only.

Do not use on damaged or broken skin.

When using this product keep out of eyes.Rinse with water to remove.

Stop use and ask a doctor if rash occurs

Keep out of reach of children if product is swallowed, get medical help or contact a Poison Control Center right away.

Uses

helps prevent sunburn
if used as directed with other sun protection measures (see Directions), decreases the risk of skin cancer and early skin aging caused by the sun

Directions

apply liberally 15 minutes before sun exposure
reapply at least every 2 hours
use a water-resistant sunscreen if swimming or sweating

Sun protection Measures. Spending time in the sun increases your risk of skin cancer and early skin aging. To decrease this risk, regulary use a sunscreen with SPF value of 15 or higher and other sun protection measures including:

limit time in the sun, especially from 10 a.m. - 2 p.m.
wear long-sleeved shirts, pants, hats and sunglasses

Other Information

protect the product in this container from excessive heat and direct sun.

Questions or Comments?

visit www.misshaus.com or call 1-888-985-9887(Ext 104)